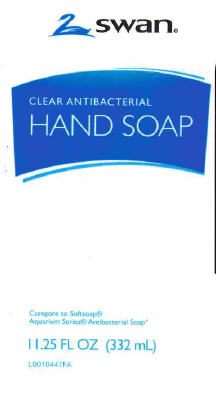 DRUG LABEL: Antibacterial Liquid Hand 
NDC: 11344-541 | Form: LIQUID
Manufacturer: Vi Jon
Category: otc | Type: HUMAN OTC DRUG LABEL
Date: 20101118

ACTIVE INGREDIENTS: TRICLOSAN .115 kg/100 L
INACTIVE INGREDIENTS: SODIUM LAURETH SULFATE; SODIUM LAURYL SULFATE; COCAMIDOPROPYL BETAINE; SODIUM CHLORIDE; DMDM HYDANTOIN; PEG-120 METHYL GLUCOSE DIOLEATE

Drug Facts

Active ingredient
Triclosan 0.115%

Purpose
Antibacterial

INDICATIONS AND USAGE

Uses for handwashing to decrease bacteria on the skin

Warnings
For external use only.

When using this product • do not get into eyes. If contact occurs, rinse eyes thoroughly with water.

Keep out of reach of children. if swallowed, get medical help or contact a Poison Control Center right away.

DOSAGE AND ADMINISTRATION

Directions •Wet hands •Apply palmful to hands •Scrub thoroughly •Rinse

INACTIVE INGREDIENT

Inactive ingredients water, sodium laureth sulfate, sodium lauryl sulfate, cocamidopropyl betaine, sodium chloride, decyl glucoside, fragrance, DMDM hydantoin, PEG-120 methyl glucose dioleate, cocamide MEA, citric acid, tetrasoidum EDTA, polyquaternium-7, PEG-7 glyceryl cocoate, D+C red no. 33, FD+C, blue no. 1

ADVERSE REACTIONS

Distributed by: Vi Jon
8515 Page Ave., St. Louis, MO. 63114

This product is not manufactured or distributed by Colgate-Palmolive Company, distributor of Softsoap Aquarium Series Antibacterial Soap

PACKAGE LABEL

Swan
CLEAR ANTIBACTERIAL
HAND SOAP
Compare to Softsoap
Aquarium Series Antibacterial Soap
11.25 FL OZ (332 mL)
Compare to Softsoap
Aquarium Series Antibacterial Soap